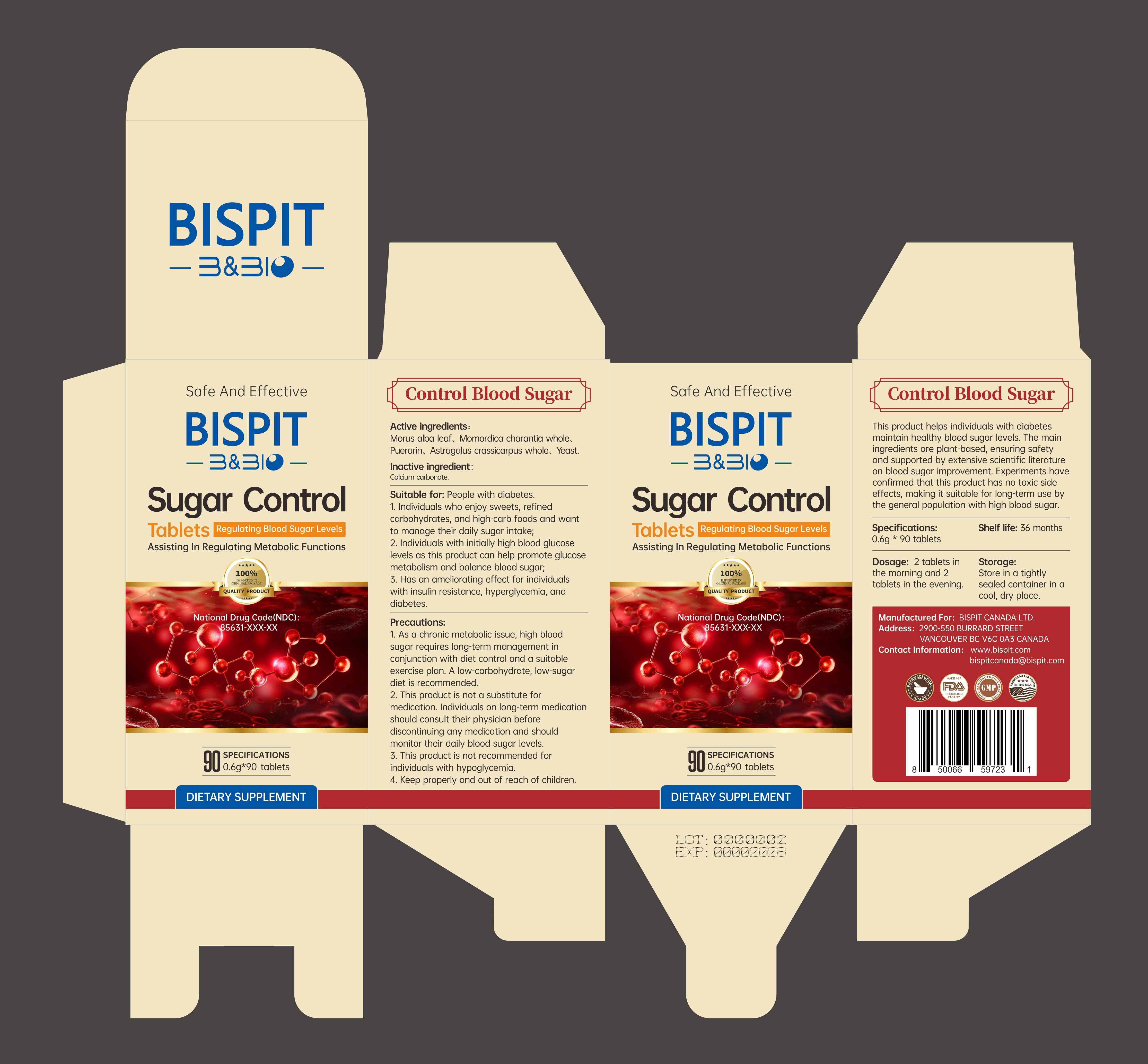 DRUG LABEL: Sugar Control
NDC: 85631-008 | Form: TABLET
Manufacturer: Bispit Canada Ltd.
Category: homeopathic | Type: HUMAN OTC DRUG LABEL
Date: 20250904

ACTIVE INGREDIENTS: ASTRAGALUS CRASSICARPUS WHOLE 132 mg/0.6 g; PUERARIN 84.6 mg/0.6 g; YEAST, UNSPECIFIED 31.8 mg/0.6 g; MORUS ALBA LEAF 232.5 mg/0.6 g; MOMORDICA CHARANTIA WHOLE 68.7 mg/0.6 g
INACTIVE INGREDIENTS: CALCIUM CARBONATE

ACTIVE INGREDIENT

Morus alba leaf、Momordica charantia whole.Puerarin、Astragalus crassicarpus whole、 Yeast.

INACTIVE INGREDIENT

Calcium carbonate.

PURPOSE

Assisting In Regulating Metabolic Functions

DOSAGE AND ADMINISTRATION

Dosage: 2 tablets inthe morning and 2tablets in the evening

Keep properly and out of reach of children.

WARNINGS

1. As a chronic metabolic issue, high bloodsugar requires long-term management inconjunction with diet control and a suitableexercise plan. A low-carbohydrate, low-sugardiet is recommended.2. This product is not a substitute formedication.Individuals on long-term medicationshould consult their physician beforediscontinuing any medication and shouldmonitor their daily blood sugar levels.3. This product is not recommended forindividuals with hypoglycemia.4. Keep properly and out of reach of children.

OTHER SAFETY INFORMATION

Storage:Store in a tightlysealed container in acool, dry place.

INDICATIONS AND USAGE

Suitable for: People with diabetes.1. individuals who enjoy sweets, refinedcarbohydrates, and high-carb foods and wantto manage their daily sugar intake;2. Individuals with initially high blood glucoselevels as this product can help promote glucosemetabolism and balance blood sugar;3. Has an ameliorating effect for individualswith insulin resistance, hyperglycemia, anddiabetes.